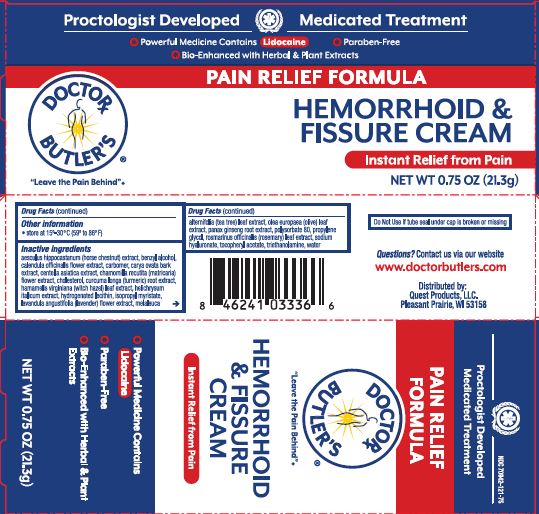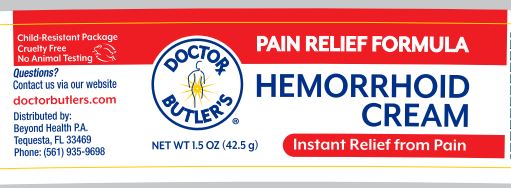 DRUG LABEL: Doctor Butlers Hemorrhoid and Fissure
NDC: 70942-121 | Form: CREAM
Manufacturer: Beyond Health, P.A.
Category: otc | Type: HUMAN OTC DRUG LABEL
Date: 20250930

ACTIVE INGREDIENTS: LIDOCAINE 5 g/100 g
INACTIVE INGREDIENTS: MELALEUCA ALTERNIFOLIA LEAF; TURMERIC; HAMAMELIS VIRGINIANA LEAF; CARYA OVATA BARK; CALENDULA OFFICINALIS FLOWER; CENTELLA ASIATICA TRITERPENOIDS; OLEA EUROPAEA LEAF; BENZYL ALCOHOL; CARBOMER 940; POLYSORBATE 80; CHOLESTEROL; HYDROGENATED SOYBEAN LECITHIN; ISOPROPYL MYRISTATE; PROPYLENE GLYCOL; WATER; TROLAMINE; .ALPHA.-TOCOPHEROL ACETATE; HORSE CHESTNUT; ASIAN GINSENG; LAVANDULA ANGUSTIFOLIA FLOWER; ROSEMARY; MATRICARIA CHAMOMILLA; HELICHRYSUM ITALICUM FLOWER; HYALURONATE SODIUM

Doctor Butler's Hemorrhoid and Fissure Cream External Pain Formula

Active Ingredient

Lidocaine USP 5.0%

Purpose

Analgesic (pain reliever)

Uses

Helps relieve the local itching and discomfort associated with anorectal disorders or inflammation.

Warnings

For external use only including the skin of the anal canal

When using this product

- avoid contact with eyes
- do not exceed recommended dosage unless directed by a doctor
- do not put this product into the rectum by using fingers or any mechanical device or applicator

Stop use and ask a doctor if

- rectal bleeding occurs
- condition worsens or does not improve within 7 days
- allergic reactions to ilgredients in this product
- symptom being treated does not subside or if redness, irritation, swelling, pain or other symptoms develop or increase

If pregnant or breast-feeding

ask a health care professional before use

Keep out of reach of children.

If swallowed, seek medical help or contact a Poison Control Cener right away.

Directions

- When practical, cleanse the area with mild soap and warm water and rinse thoroughly. Gently dry by patting or blotting with toilet tissue or soft cloth before applying.
- Adults and children 12 years and older: apply externally to the affected area up to 6 times a day.
- Children under 12 years of age: consult a doctor.

Other information

- store at 15º-30º C (59ºto 86º F)

Inactive ingredients

Aesculus Hippocastanum (Horse Chestnut) Extract, Benzyl Alcohol, Calendula Officinalis Flower Extract, Carbomer, Carya Ovata Bark Extract, Centella Asiatica Extract, Chamomilla Recutita (Matricaria) Flower Extract, Cholesterol, Curcuma Longa (Turmeric) Root Extract, Hamamelis Virginiana (Witch Hazel) Leaf Extract, Helichrysum Italicum Extract, Hydrogenated Lecithin, Isopropyl Myristate, Lavandula Angustifolia (Lavender) Flower Extract, Melaleuca Alternifolia (Tea Tree) Leaf Extract, Olea Europaea (Olive) Leaf Extract, Panax Ginseng Root Extract, Polysorbate 80, Propylene Glycol, Rosmarinus Officinalis (Rosemary) Leaf Extract, Sodium Hyaluronate, Tocopheryl Acetate, Triethanolamine, Water.